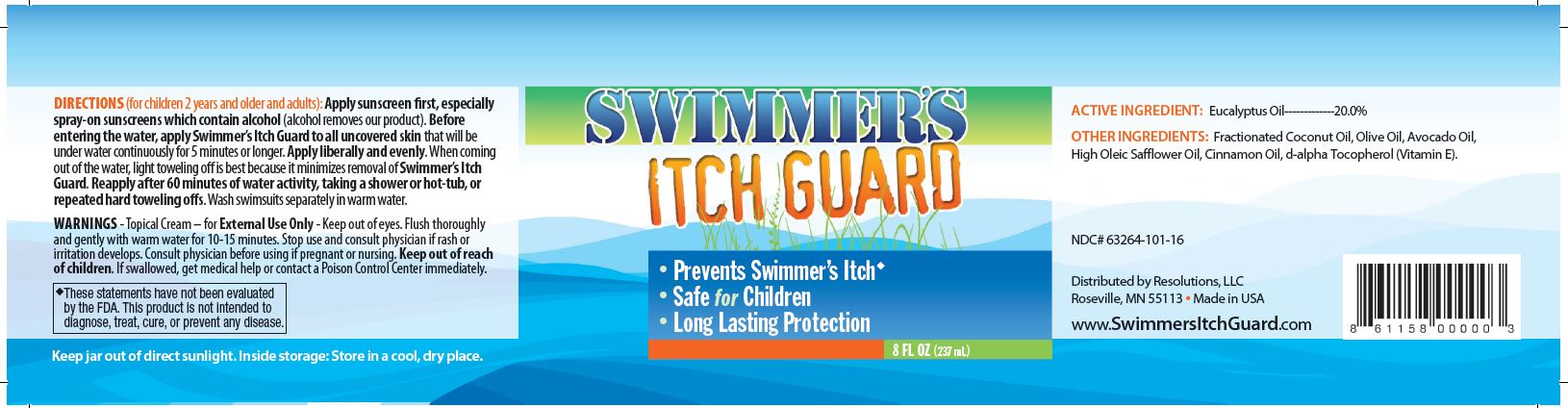 DRUG LABEL: SWIMMERS ITCH GUARD
NDC: 63264-102 | Form: OIL
Manufacturer: RESOLUTIONS LLC
Category: homeopathic | Type: HUMAN OTC DRUG LABEL
Date: 20220217

ACTIVE INGREDIENTS: EUCALYPTUS OIL 20 g/100 mL
INACTIVE INGREDIENTS: MEDIUM-CHAIN TRIGLYCERIDES; OLIVE OIL; SAFFLOWER OIL; .ALPHA.-TOCOPHEROL ACETATE, D-; AVOCADO OIL; CINNAMON OIL

RESOLUTIONS - SWIMMER'S ITCH GUARD (63264-102)

ACTIVE INGREDIENT

EUCALYPTUS OIL 20%

PURPOSE

SKIN PROTECTANT

USES

- PREVENT SWIMMER'S ITCH
- SAFE FOR CHILDREN
- LONG LASTING PROTECTION

WARNINGS

TOPICAL CREAM - FOR EXTERNAL USE ONLY - KEEP OUT OF EYES. FLUSH THOROUGHLY AND GENTLY WITH WARM WATER FOR 10-15 MINUTES. STOP USE AND CONSULT PHYSICIAN IF RASH OR IRRITATION DEVELOPS. CONSULT PHYSICIAN BEFORE USING IF PREGNANT OR NURSING.

KEEP OUT OF REACH OF CHILDREN. IF SWALLOWED, GET MEDICAL HELP OR CONTACT A POISON CONTROL CENTER IMMEDIATELY.

DIRECTIONS (FOR CHILDREN 2 YEARS AND OLDER AND ADULTS):

Apply sunscreen first, especially spray-on sunscreens which contain alcohol (alcohol removes our product). Before entering the water, apply Swimmer’s Itch Guard to all uncovered skin that will be under water continuously for 5 minutes or longer. Apply liberally and evenly. When coming out of the water, light toweling off is best because it minimizes removal of Swimmer’s Itch Guard. Reapply after 60 minutes of water activity, taking a shower or hot-tub, or repeated hard toweling offs. Wash swimsuits separately in warm water.

OTHER INGREDIENTS:

Fractionated Coconut Oil, Olive Oil, Avocado Oil, High Oleic Safflower Oil, Cinnamon Oil, d-alpha Tocopherol (Vitamin E).